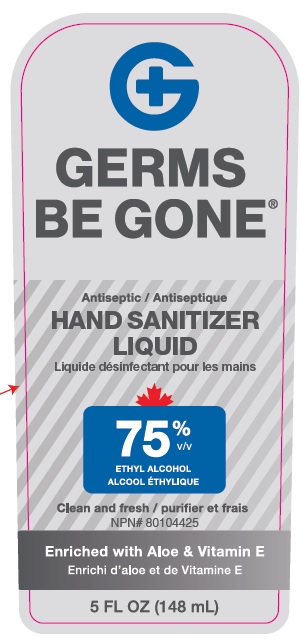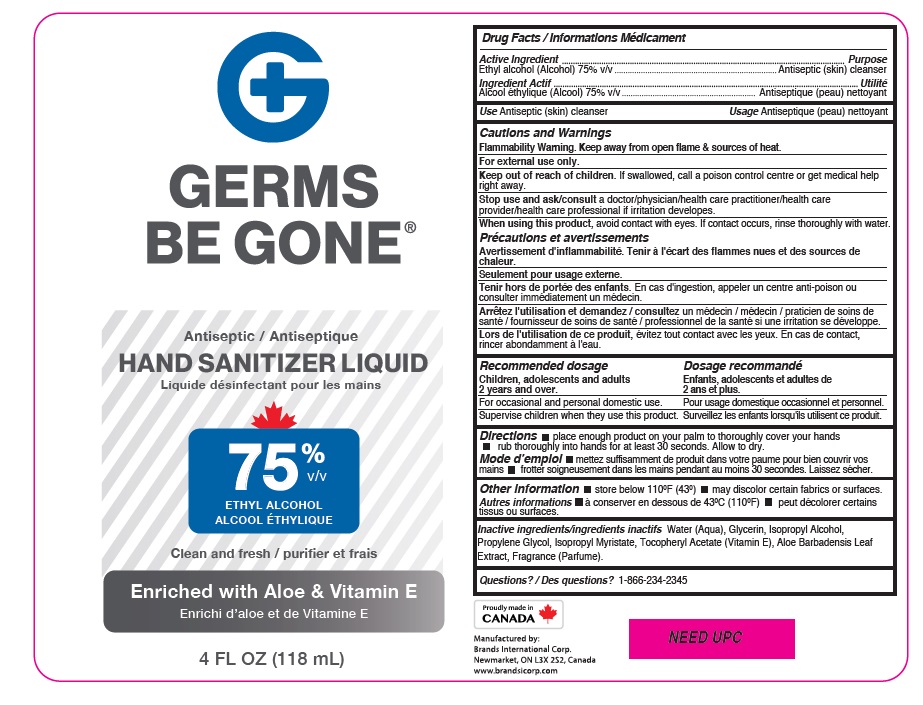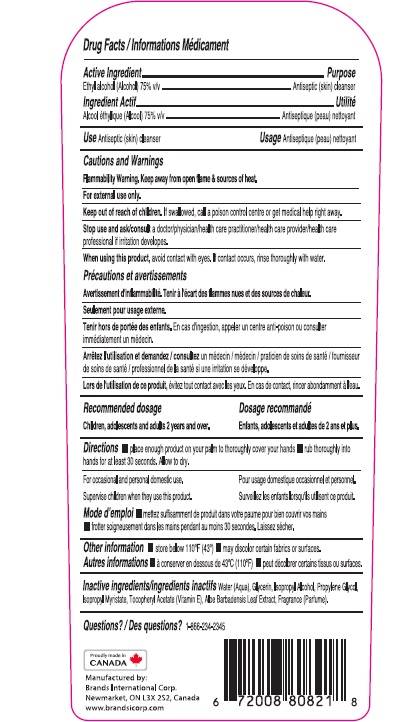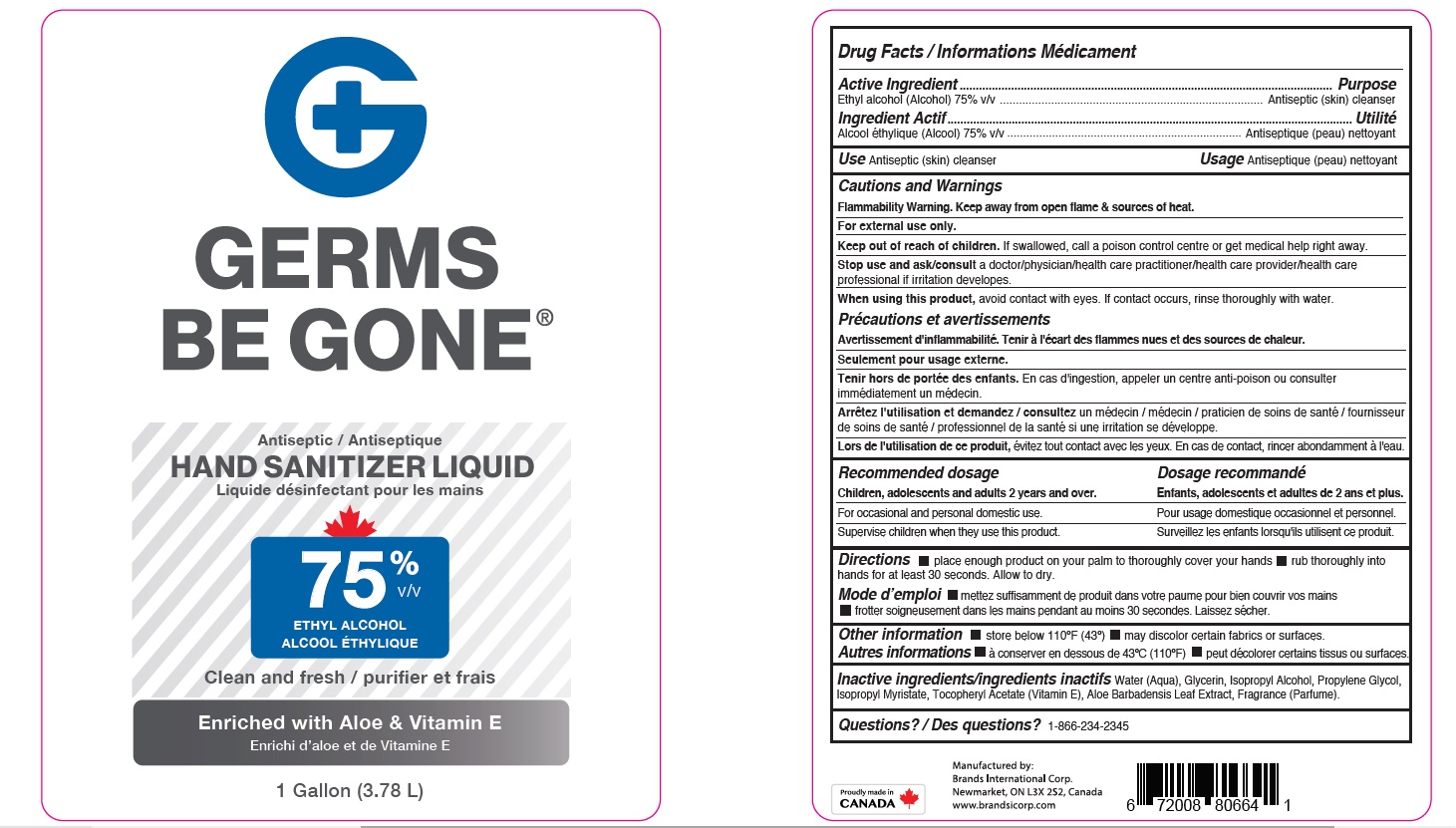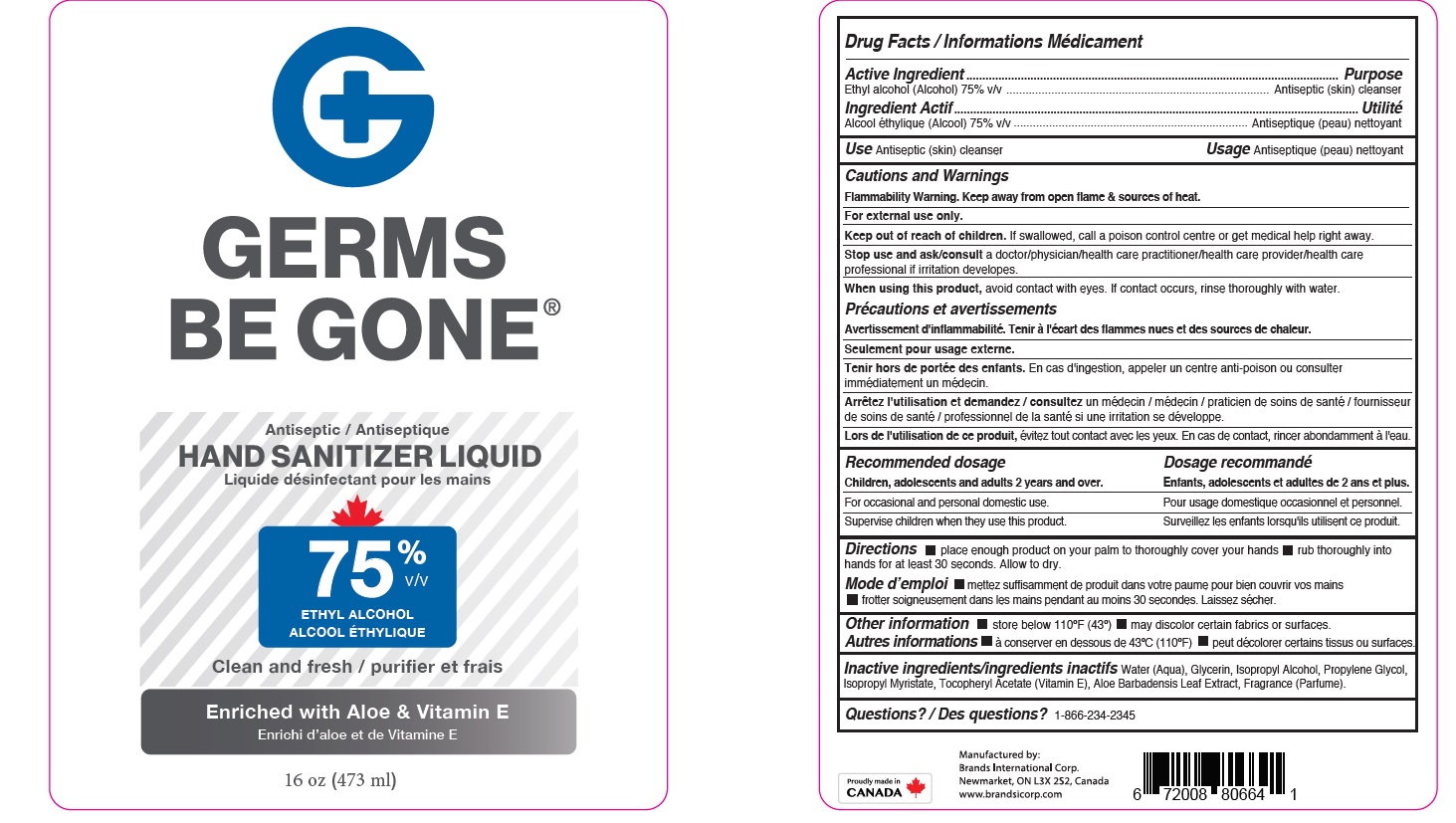 DRUG LABEL: Germs be gone hand Sanitizer
NDC: 50157-507 | Form: LIQUID
Manufacturer: Brands International
Category: otc | Type: HUMAN OTC DRUG LABEL
Date: 20210407

ACTIVE INGREDIENTS: ALCOHOL 75 mL/100 mL
INACTIVE INGREDIENTS: ISOPROPYL MYRISTATE; ISOPROPYL ALCOHOL; WATER; PROPYLENE GLYCOL; CARBOMER INTERPOLYMER TYPE A (ALLYL SUCROSE CROSSLINKED); GLYCERIN; ALOE VERA LEAF; AMINOMETHYLPROPANOL; PEG-40 CASTOR OIL; EDETATE DISODIUM; .ALPHA.-TOCOPHEROL ACETATE

Germs Be Gone Hand sanitizer

Drug Facts

Active Ingredient

Ethyl Alcohol, 75% v/v

Purpose

Antiseptic

Uses

- instant hand antiseptic to decrease bacteria on the skin

Warnings

For external use only. Flammable, keep away from fire or flame.

When using this product keep out of eyes. If contact with eyes occurs, rinse promptly and thoroughly with water.

Stop use and ask a doctor if significant irritation or sensitization develops.

Keep out of reach of children. If swallowed, get medical help or contact a Poison Control Center right away.

Directions

Apply to clean, dry hands. Apply sufficient amount to thoroughly wet all surfaces of hands and fingers. Rub onto hands until dry.

- Supervise children in the use of this product.

Other Information

Store below 43°C (110°F)

Inactive Ingredients

carbomer, aloe barbadensis leaf juice, aminomethyl propanol, disodium EDTA, glycerin, PEG-40, propylene glycol, water, isopropyl myristate, tocopheryl acetate (Vit E)., isopropyl alcohol

Please see label on the container.

QUESTIONS

1-866-234-2345